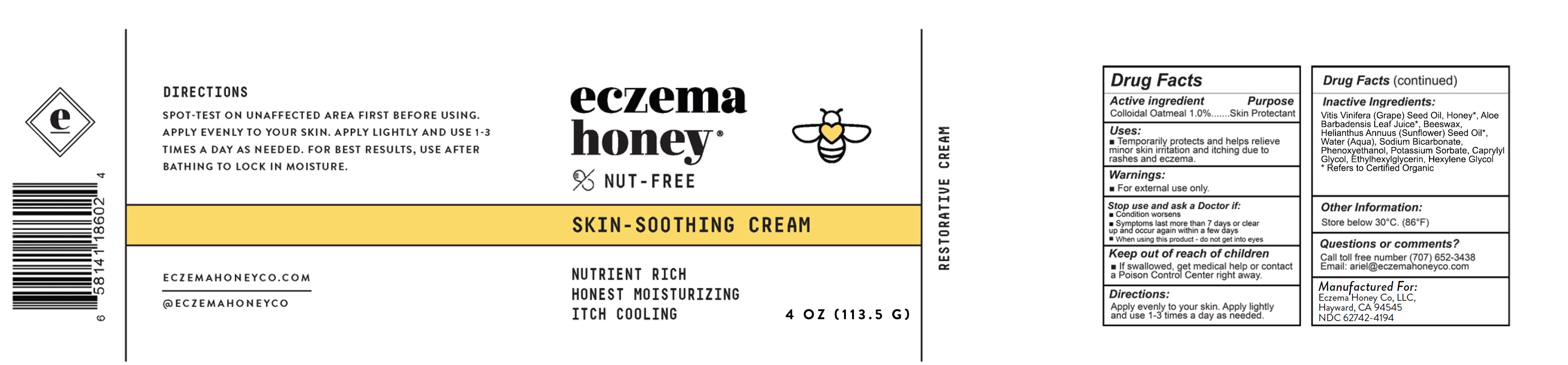 DRUG LABEL: Skin Soothing Cream - Nut Free
NDC: 62742-4194 | Form: CREAM
Manufacturer: Allure Labs
Category: otc | Type: HUMAN OTC DRUG LABEL
Date: 20241205

ACTIVE INGREDIENTS: OATMEAL 1 mg/1 g
INACTIVE INGREDIENTS: POTASSIUM SORBATE; CAPRYLYL GLYCOL; ETHYLHEXYLGLYCERIN; PHENOXYETHANOL; HEXYLENE GLYCOL; WATER; GRAPE SEED OIL; ALOE VERA LEAF; YELLOW WAX; HONEY; SODIUM BICARBONATE; SUNFLOWER OIL

Drug Facts

Active Ingredient: Colloidal Oatmeal 1.0%

Purpose: Skin Protectant

Uses:

- Temporarily protects and helps relieve minor skin iritation and itching due to rashes and eczema.

Warning:

- For external use only.

Stop use and ask a Doctor if:

- Condition worsens
- Symptoms last more than 7 days or clear up and occur again within few days

When using this product - do not get into eyes.

Keep out of reach of children

- If swallowed, get medical help or contact a Poison Control Center right away.

Directions:

Apply evenly to your skin. Apply lightly and use 1-3 times a day as needed.

INACTIVE INGREDIENT

Vitis Vinifera (Grape) Seed Oil, Honey*, Aloe Barbadensis Leaf Juice*, Beeswax, Helianthus Annus (sunflower) seed oil*, Water (Aqua), Sodium Bicarbonate, Phenoxyethanol, Potassium Sorbate, Caprylyl Glycol, Ethylhexylglycerin, Hexylene Glycol

* Refers to Certified Organics.

Other Information:

Store Below 30ºC. (86ºF)

Questions or comments?

Call to toll free number (707) 652-3438

email: ariel@eczemahoneyco.com

PACKAGE LABEL

Manufactured for:

Eczema Honey Co, LLC

Hayward CA-94544